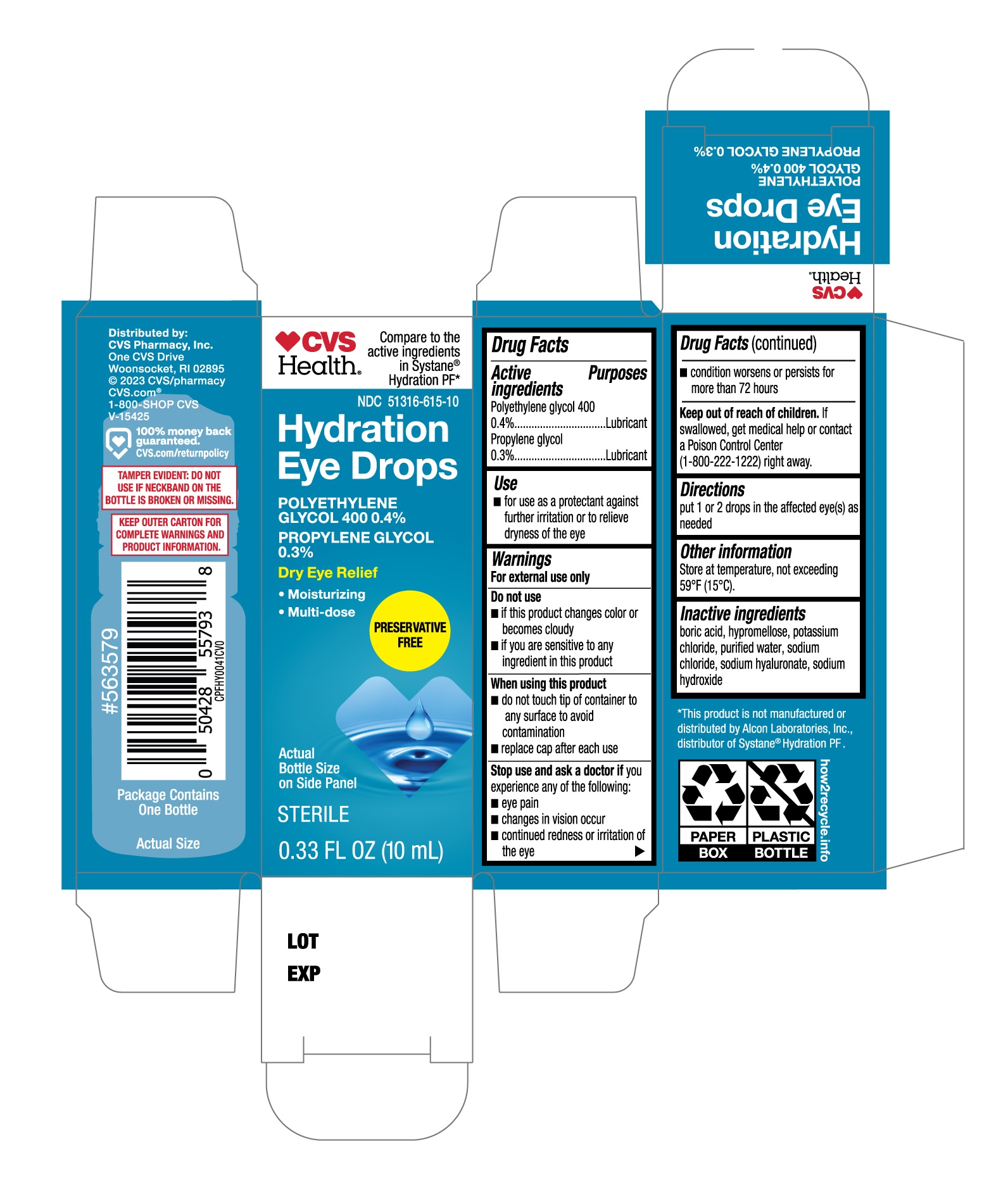 DRUG LABEL: CVS Hydration Eye Drops
NDC: 51316-615 | Form: SOLUTION/ DROPS
Manufacturer: CVS
Category: otc | Type: HUMAN OTC DRUG LABEL
Date: 20251230

ACTIVE INGREDIENTS: PROPYLENE GLYCOL 0.3 g/100 mL; POLYETHYLENE GLYCOL 400 0.4 g/100 mL
INACTIVE INGREDIENTS: BORIC ACID; POTASSIUM CHLORIDE; WATER; SODIUM HYDROXIDE; HYPROMELLOSE, UNSPECIFIED; SODIUM CHLORIDE; HYALURONATE SODIUM

CVS Hydration Eye Drops 10 mL (PLD)

Active ingredients

Polyethylene glycol 400 0.4%

Propylene glycol 0.3%

Purposes

Lubricant

Lubricant

Use

- for use as a protectant against further irritation or to relieve dryness of the eye

Warnings

For external use only

Do not use

- if this product changes color or becomes cloudy
- if you are sensitive to any ingredient in this product

When using this product

- do not touch the tip of container to any surface to avoid contamination
- replace cap after each use

Stop use and ask a doctor

if you experience any of the following:

- eye pain
- changes in vision occur
- continued redness or irritation of the eye
- condition worsens or persists for more than 72 hours

Keep out of reach of childeren.

If swallowed, get medical help or contact a Poison Control Center (1-800-222-1222) right away.

Directions

put 1 or 2 drops in the affected eye(s) as needed

Other information

Store at temperature, not exceeding 59°F (15°C)

Inactive ingredients

boric acid, hypromellose, potassium chloride, purified water, sodium chloride, sodium hyaluronate, sodium hydroxide